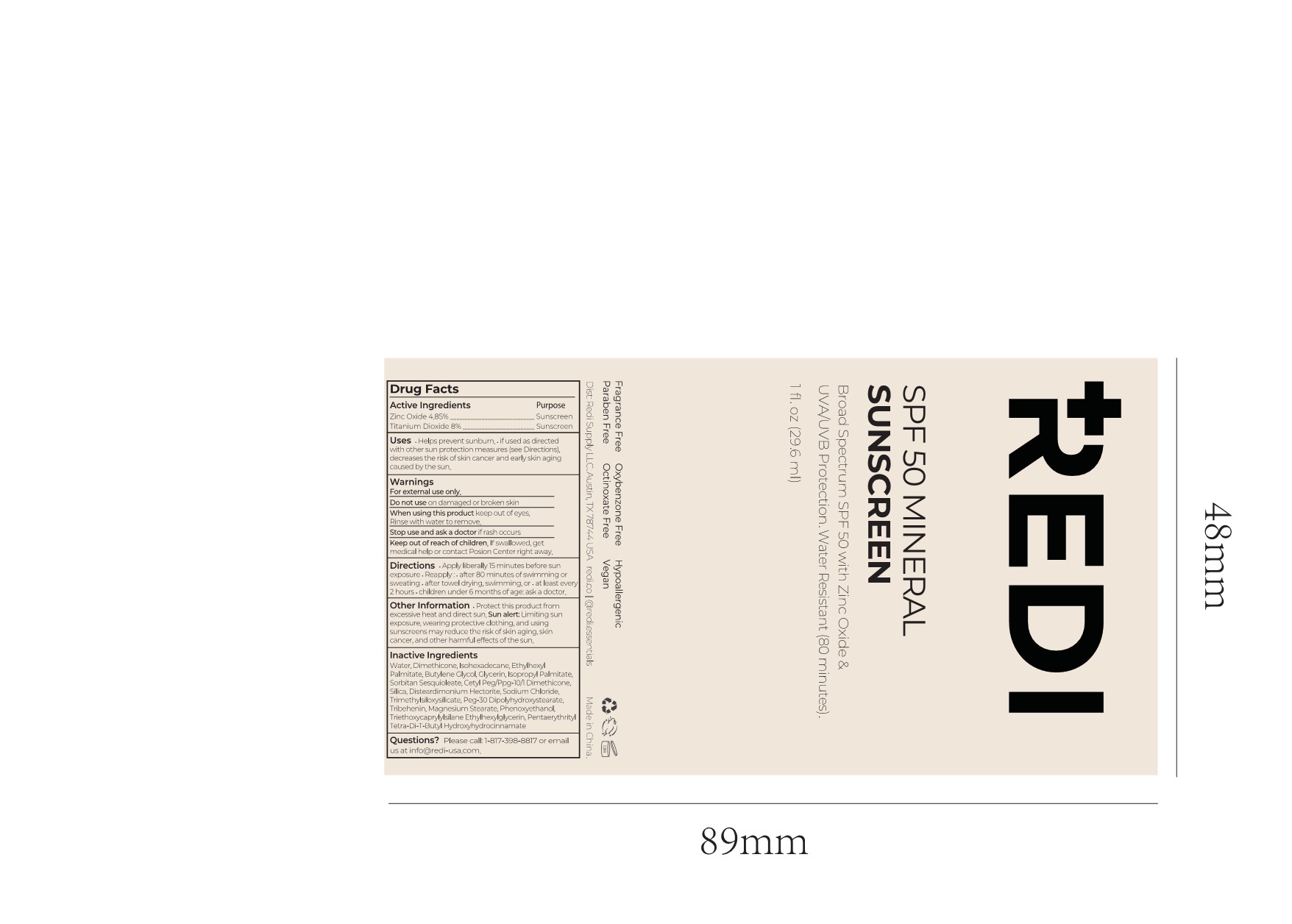 DRUG LABEL: SPF 50 MINERAL SUNSCREEN LIP
NDC: 84066-104 | Form: CREAM
Manufacturer: Guangzhou Tata Biotechnology Co., Ltd.
Category: otc | Type: HUMAN OTC DRUG LABEL
Date: 20251222

ACTIVE INGREDIENTS: ZINC OXIDE 4.85 mg/100 mL; TITANIUM DIOXIDE 8 mg/100 mL
INACTIVE INGREDIENTS: WATER; PENTAERYTHRITOL TETRAKIS(3-(3,5-DI-TERT-BUTYL-4-HYDROXYPHENYL)PROPIONATE); SORBITAN SESQUIOLEATE; ISOPROPYL PALMITATE; SILICON DIOXIDE; ETHYLHEXYL PALMITATE; TRIMETHYLSILOXYSILICATE (M/Q 0.8-1.0); DISTEARDIMONIUM HECTORITE; DIMETHICONE; BUTYLENE GLYCOL; TRIETHOXYCAPRYLYLSILANE; ISOHEXADECANE; GLYCERIN; CETYL PEG/PPG-10/1 DIMETHICONE (HLB 2); SODIUM CHLORIDE; PEG-30 DIPOLYHYDROXYSTEARATE; TRIBEHENIN; MAGNESIUM STEARATE; PHENOXYETHANOL; ETHYLHEXYLGLYCERIN

SPF 50 MINERAL SUNSCREEN LIP

ACTIVE INGREDIENT

Zinc Oxide 4.85%
Titanium Dioxide 8%

PURPOSE

Sunscreen

INDICATIONS AND USAGE

Helps prevent sunburn.

if used as directed with other sun protection measures (see Directions)decreases the risk of skin cancer and early skin agingcaused by the sun.

WARNINGS

For external use only.

Do not use on damaged or broken skin

When using this product keep out of eyes.

Rinse with water to remove.

Stop use and ask a doctor if rash occurs.

Keep out of reach of children.lf swallowed, getmedical help or contact Posion Center right away.

Directions

·Applyliberally15 minutes before sun exposure·Reapply:·after 80 minutes of swimming orsweating·after towel drying, swimming, or·at least every 2 hours ·children under 6 months of age: ask a doctor.

OTHER SAFETY INFORMATION

.Protect this product from excessive heat and direct sun.Sun alert: Limiting sunexposure, wearing protective clothing, and using sunscreens may reduce the risk of skin aging, skin cancer,and other harmful effects ofthe sun.

INACTIVE INGREDIENT

Water,Dimethicone, lsohexadecane, EthylhexylPalmitate, Butylene Glycol, Glycerin, lsopropyl PalmitateSorbitan Sesquioleate, Cetyl Peg/Ppg-10/ Dimethicone.Silica, Disteardimonium Hectorite, Sodium Chloride,Trimethylsiloxysilicate, Peg-30 Dipolyhydroxystearate,

Tribehenin, Magnesium Stearate, Phenoxyethanol,Triethoxycaprylylsilane Ethylhexylglycerin, PentaerythrityTetra-Di-T-Buty Hydroxyhydrocinnamate

QUESTIONS

Please call:1-817-398-8817 or emus at info@redi-usa.com.